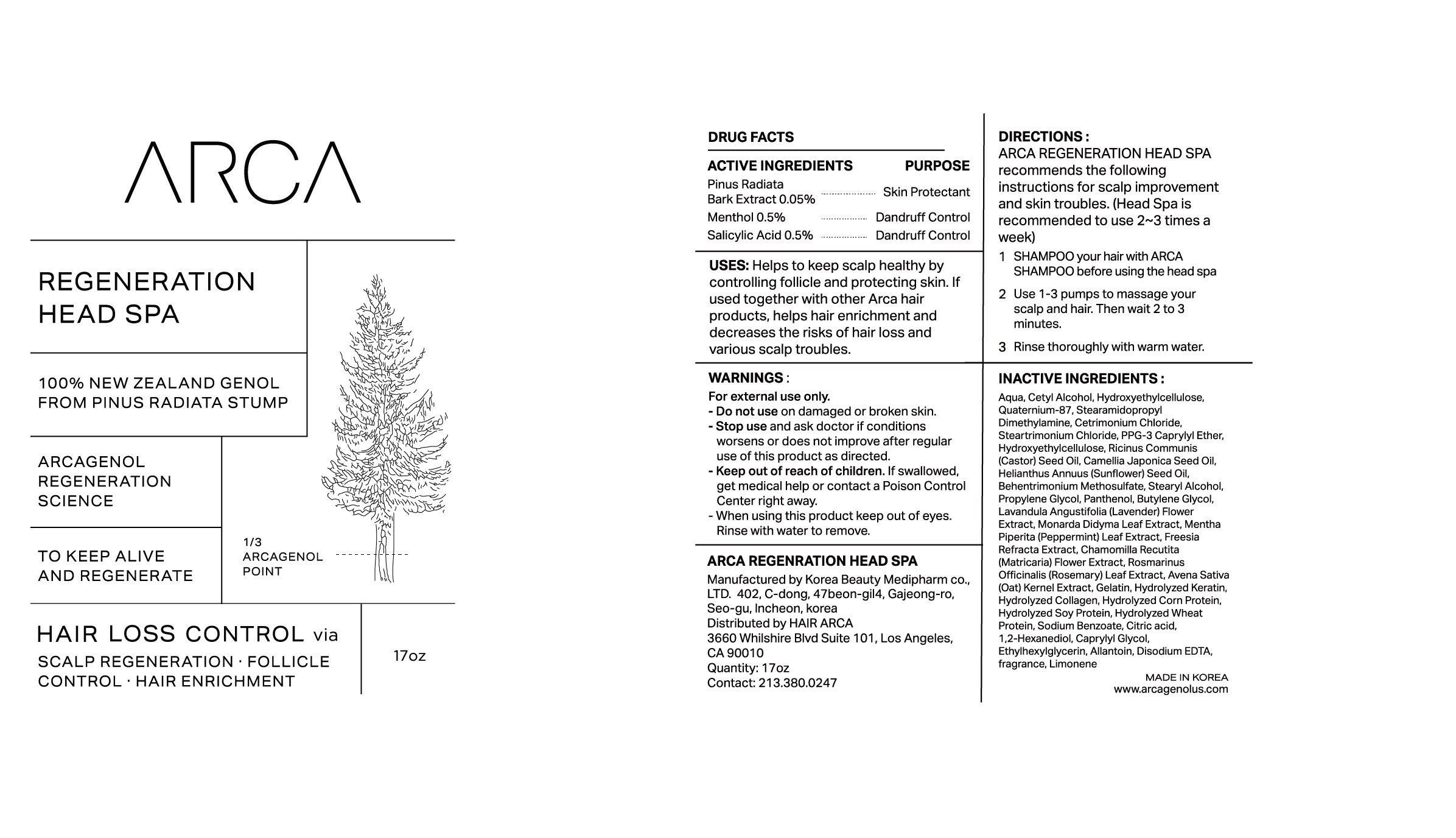 DRUG LABEL: ARCA Regeneration Head Spa
NDC: 83104-301 | Form: SHAMPOO
Manufacturer: Hair Arca, Inc
Category: otc | Type: HUMAN OTC DRUG LABEL
Date: 20220929

ACTIVE INGREDIENTS: SALICYLIC ACID 0.5 g/100 mL
INACTIVE INGREDIENTS: CITRIC ACID MONOHYDRATE; STEARYL ALCOHOL; PROPYLENE GLYCOL; MONARDA DIDYMA LEAF; MENTHA PIPERITA LEAF; CHAMOMILE; ROSEMARY; FREESIA ALBA WHOLE; ETHYLHEXYLGLYCERIN; OAT; PPG-10 CAPRYLYL ETHER; CASTOR OIL; SUNFLOWER OIL; BEHENTRIMONIUM METHOSULFATE; PANTHENOL; HYDROXYETHYL CELLULOSE, UNSPECIFIED; GELATIN; HYDROLYZED WHEAT PROTEIN (ENZYMATIC, 3000 MW); EDETATE DISODIUM ANHYDROUS; CAMELLIA JAPONICA SEED OIL; HYDROLYZED SOY PROTEIN (ENZYMATIC; 2000 MW); CETRIMONIUM CHLORIDE; WATER; TRIMETHYL OCTADECYL AMMONIUM CHLORIDE; LAVANDULA ANGUSTIFOLIA SUBSP. ANGUSTIFOLIA FLOWER; CETYL ALCOHOL; STEARAMIDOPROPYL DIMETHYLAMINE; SODIUM BENZOATE; 1,2-HEXANEDIOL; ALLANTOIN; BUTYLENE GLYCOL; CAPRYLYL GLYCOL

83104-301 ARCA Regeneration Head Spa

Active ingredients

Pinus Radiata Bark Extract 0.05%

Menthol 0.5%

Salicylic Acid 0.5%

Purpose

Pinus Radiata Bark Extract 0.05% - Skin Protectant

Menthol 0.5% - Dandruff Control

Salicylic Acid 0.5% - Dandruff Control

Uses

Helps to keep scalp healthy by controlling follicle and protecting skin.

If used together with other Arca hair products, helps hair enrichment and decreases the risks of hair loss and various scalp troubles.

Warnings

For external use only.

Warnings

When using this product keep out of eyes.

Rinse with water to remove.

Warnings

Stop use and ask doctor if conditions worsens or does not improve after regular use of this product as directed.

Warnings

Keep out of reach of children. If swallowed, get medical help or contact a Poison Control Center right away.

Warnings

Do not use on damaged or broken skin.

Directions

ARCA REGENERATION HEAD SPA recommends the following instructions for scalp improvement and skin troubles.

(Head Spa is recommended to use 2~3 times a week)

1 SHAMPOO your hair with ARCA SHAMPOO before using the head spa

2 Use 1-3 pumps to massage your scalp and hair. Then wait 2 to 3 minutes.

3 Rinse thoroughly with warm water.

Inactive Ingredients

Aqua, Cetyl Alcohol, Hydroxyethylcellulose, Quaternium-87, Stearamidopropyl Dimethylamine, Cetrimonium Chloride, Steartrimonium Chloride, PPG-3 Caprylyl Ether, Hydroxyethylcellulose, Ricinus Communis(Castor) Seed Oil, Camellia Japonica Seed Oil, Helianthus Annuus (Sunflower) Seed Oil, Behentrimonium Methosulfate, Stearyl Alcohol, Propylene Glycol, Panthenol, Butylene Glycol, Lavandula Angustifolia (Lavender) Flower Extract, Monarda Didyma Leaf Extract, Mentha Piperita (Peppermint) Leaf Extract, Freesia

Refracta Extract, Chamomilla Recutita(Matricaria) Flower Extract, Rosmarinus Officinalis (Rosemary) Leaf Extract, Avena Sativa

(Oat) Kernel Extract, Gelatin, Hydrolyzed Keratin, Hydrolyzed Collagen, Hydrolyzed Corn Protein, Hydrolyzed Soy Protein, Hydrolyzed Wheat Protein, Sodium Benzoate, Citric acid, 1,2-Hexanediol, Caprylyl Glycol, Ethylhexylglycerin, Allantoin, Disodium EDTA,

fragrance, Limonene

Display panel

83104-401